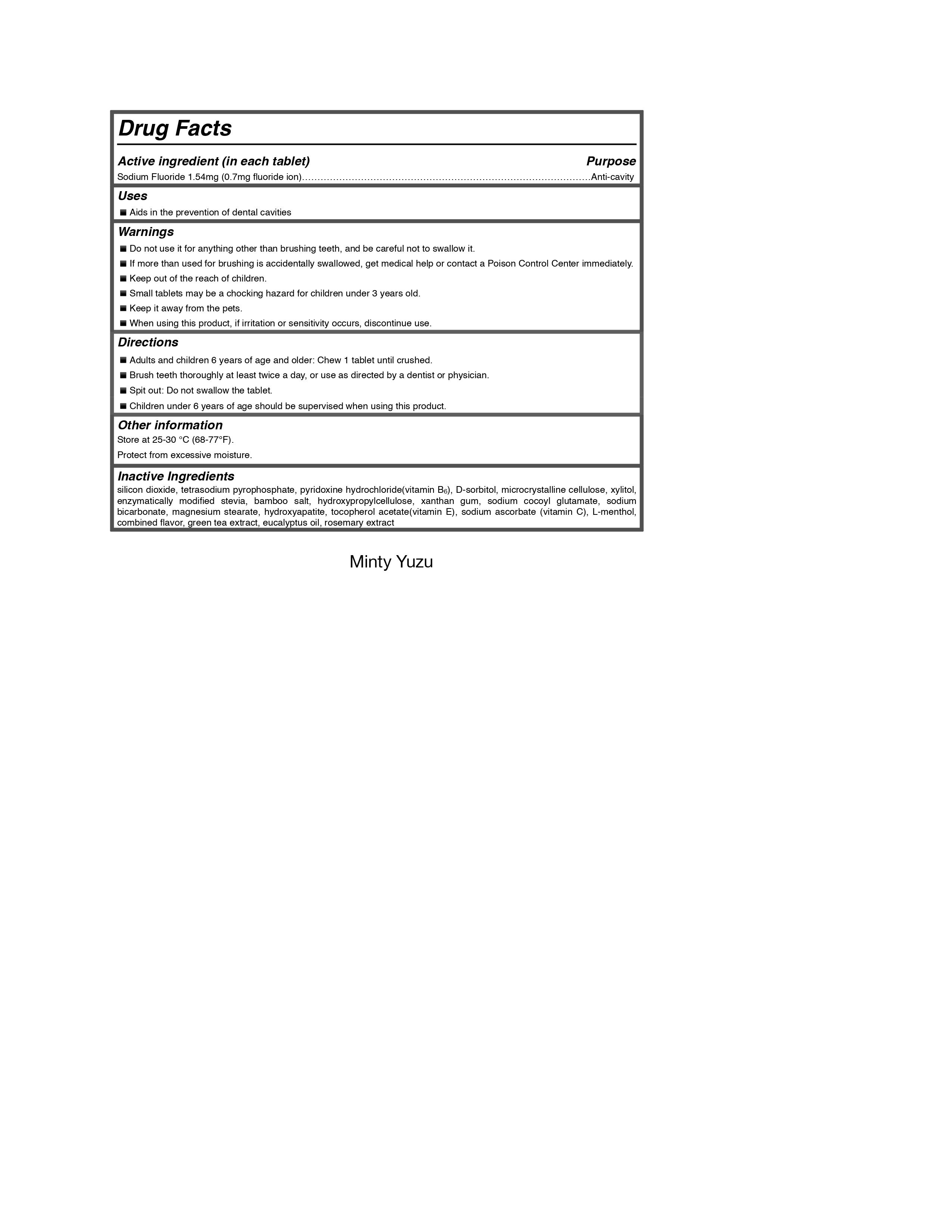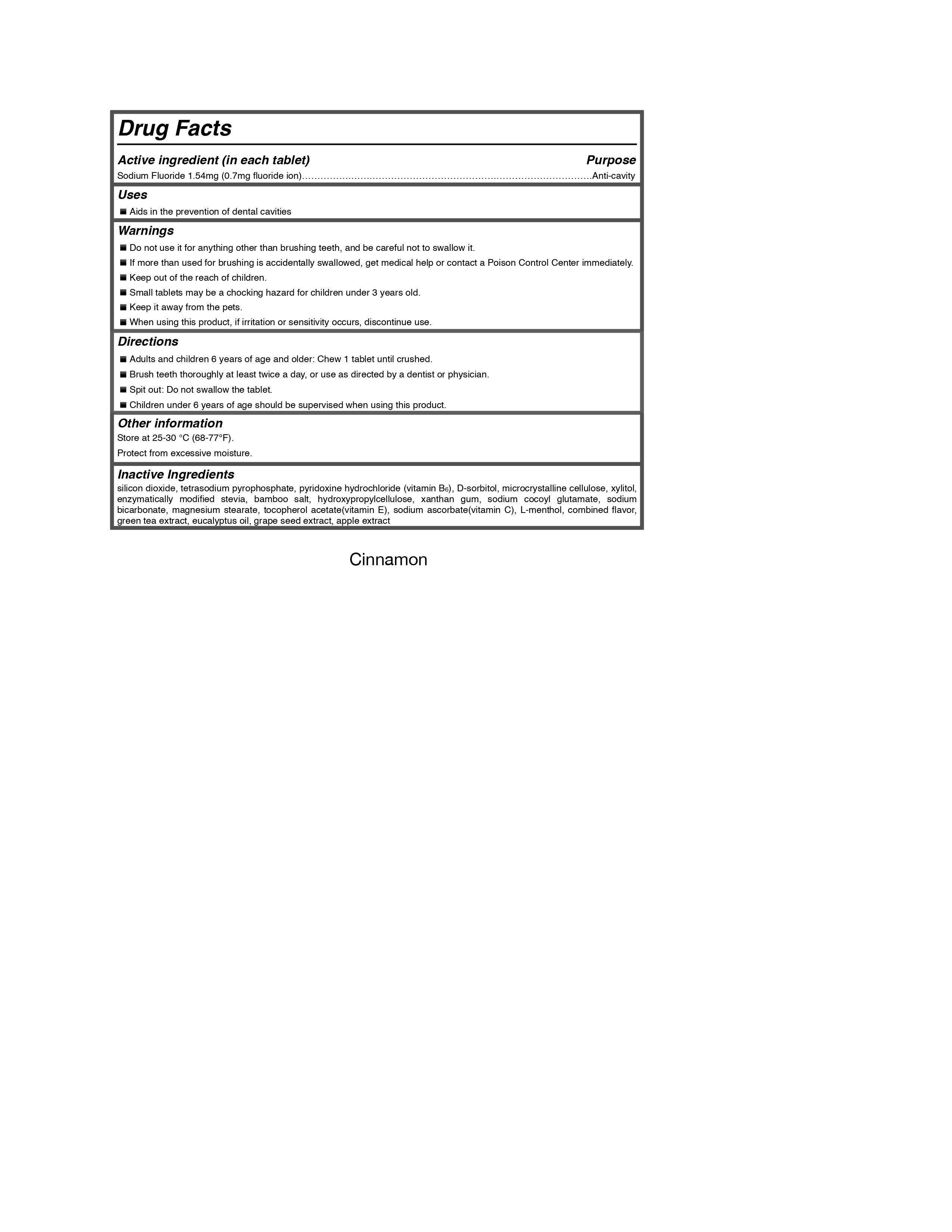 DRUG LABEL: TIDALOVE SMILE MORE ORAL CARE
NDC: 82756-001 | Form: TABLET
Manufacturer: Paranmare
Category: otc | Type: HUMAN OTC DRUG LABEL
Date: 20221208

ACTIVE INGREDIENTS: SODIUM FLUORIDE 0.7 mg/1.54 mg
INACTIVE INGREDIENTS: PYRIDOXINE HYDROCHLORIDE; SORBITOL; EUCALYPTUS OIL; SILICON DIOXIDE; SODIUM PYROPHOSPHATE; XYLITOL; ROSEMARY; SEA SALT; HYDROXYPROPYL CELLULOSE, UNSPECIFIED; SODIUM COCOYL GLUTAMATE; SODIUM BICARBONATE; .ALPHA.-TOCOPHEROL ACETATE; MENTHOL, UNSPECIFIED FORM; MICROCRYSTALLINE CELLULOSE; XANTHAN GUM; MAGNESIUM STEARATE; SODIUM ASCORBATE; GREEN TEA LEAF

Active Ingredients(in each tablet) purpose

Sodium fluoride 1.54mg (0.7mg fluoride ion) anticavity

Inactive Ingredients

silicon dioxide, tetrasodium pyrophosphate, pyridoxine hydrochloride(vitamin B6), D-sorbitol, microcrystalline cellulose, xylitol, enzymatically modified stevia, bamboo salt, hydroxypropylcellulose, xanthan gum, sodium cocoyl glutamate, sodium bicarbonate, magnesium stearate, hydroxyapatite, tocopherol acetate(vitamin E), sodium ascorbate (vitamin C), L-menthol, combined flavor, green tea extract, eucalyptus oil, rosemary extract

PURPOSE

Aids in the prevention of dental cavities

WHEN USING

▪ Adults and children 6 years of age and older: Chew 1 tablet until crushed.
▪ Brush teeth thoroughly at least twice a day, or use as directed by a dentist or physician.

▪ Spit out: Do not swallow the tablet.
▪ Children under 6 years of age should be supervised when using this product.

Keep out of the reach of children.

ASK DOCTOR

Brush teeth thoroughly at least twice a day, or use as directed by a dentist or physician.

If more than used for brushing is accidentally swallowed, get medical help or contact a Poison Control Center immediately.

Do not use it for anything other than brushing teeth, and be careful not to swallow it.
If more than used for brushing is accidentally swallowed, get medical help or contact a Poison Control Center immediately.Keep out of the reach of children.

Small tablets may be a chocking hazard for children under 3 years old.
Keep it away from the pets.
When using this product, if irritation or sensitivity occurs, discontinue use.

When using this product, if irritation or sensitivity occurs, discontinue use.

OTHER SAFETY INFORMATION

Store at 25-30 °C (68-77°F). Protect from excessive moisture.

DOSAGE AND ADMINISTRATION

Gently chew 1 tablet until it crushed. Brush teeth thoroughly,

INDICATIONS AND USAGE

Adults and children 6 years of age and older: Chew 1 tablet until crushed.
Brush teeth thoroughly at least twice a day, or use as directed by a dentist or physician.

Spit out: Do not swallow the tablet.
Children under 6 years of age should be supervised when using this product.